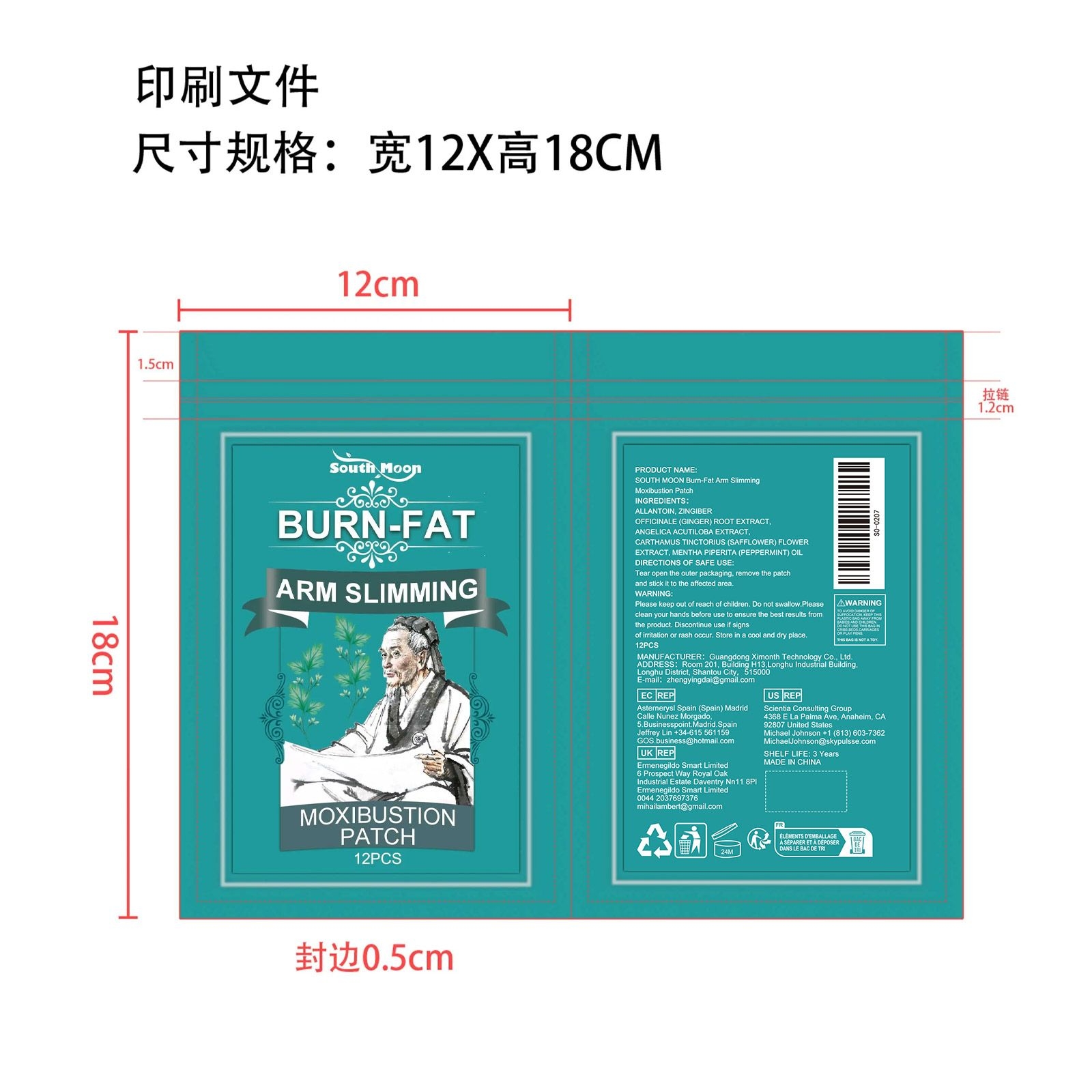 DRUG LABEL: Bum-Fat Arm Slimming Moxibustion Patch
NDC: 84660-020 | Form: PATCH
Manufacturer: Guangdong Ximonth Technology Co., Ltd.
Category: otc | Type: HUMAN OTC DRUG LABEL
Date: 20240921

ACTIVE INGREDIENTS: SAFFLOWER 4.05 g/27 g; ANGELICA ACUTILOBA WHOLE 5.4 g/27 g; GINGER 6.75 g/27 g
INACTIVE INGREDIENTS: ALLANTOIN 8.1 g/27 g; PEPPERMINT OIL 2.7 g/27 g

Active Ingredient(s)

ZINGIBER OFFICINALE (GINGER) ROOT EXTRACT、ANGELICA ACUTILOBA EXTRACT、CARTHAMUS TINCTORIUS (SAFFLOWER) FLOWER EXTRACT、MENTHA PIPERITA (PEPPERMINT) OIL

Purpose

Relieves joint pain

Use

Tear open the outer packaging, remove the patch and stick it to the affected area.

Warnings

Please keep out of reach of children.Do not swallow.Please clean your hands before use to ensure the best results from the product.Discontinue use if signs of irritation or rash occur.Store in a cool and dry place.

Do not use

Discontinue use if signs of irritation or rash occur.

STOP USE

Discontinue use if signs of irritation or rash occur.

STORAGE AND HANDLING

Avoid freezing and excessive heat above 40C (104F) ）
Store in a cool and dry place.

KEEP OUT OF REACH OF CHILDREN

Please keep out of reach of children. Do not swallow.

INACTIVE INGREDIENT

ALLANTOIN